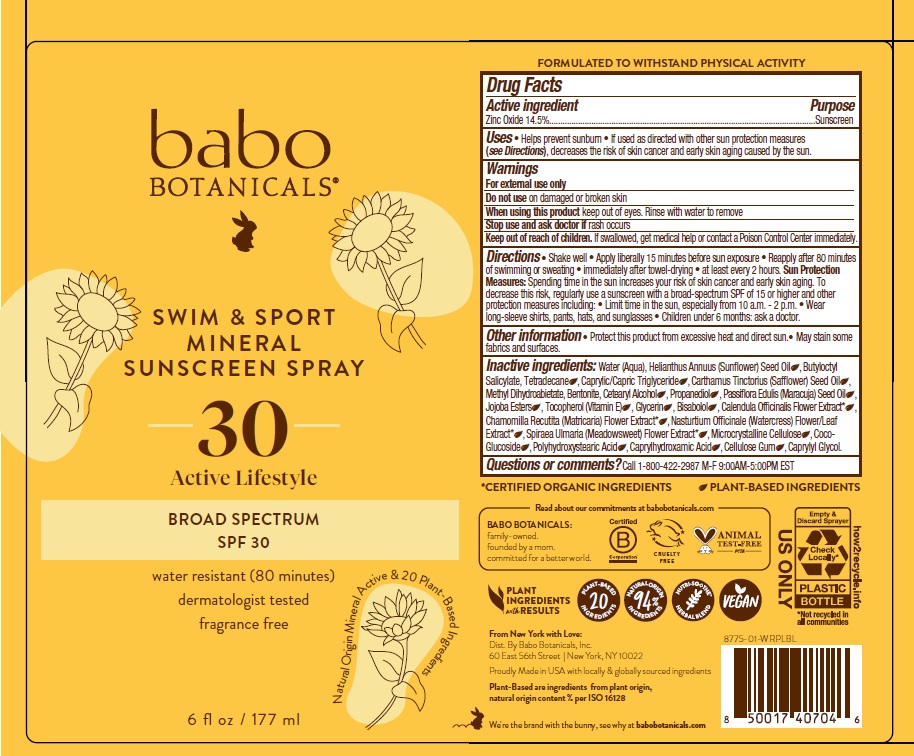 DRUG LABEL: Babo Botanicals Swim and Sport Mineral Sunscreen SPF 30
NDC: 79265-8775 | Form: SPRAY
Manufacturer: Babo Botanicals, Inc.
Category: otc | Type: HUMAN OTC DRUG LABEL
Date: 20241212

ACTIVE INGREDIENTS: ZINC OXIDE 145 mg/1 mL
INACTIVE INGREDIENTS: CAPRYLYL GLYCOL; POLYHYDROXYSTEARIC ACID (2300 MW); BENTONITE; CAPRYLHYDROXAMIC ACID; METHYL DIHYDROABIETATE; FILIPENDULA ULMARIA FLOWER; PASSIFLORA EDULIS SEED OIL; JOJOBA OIL; CETOSTEARYL ALCOHOL; CARBOXYMETHYLCELLULOSE SODIUM, UNSPECIFIED FORM; SUNFLOWER OIL; BUTYLOCTYL SALICYLATE; MEDIUM-CHAIN TRIGLYCERIDES; SAFFLOWER OIL; PROPANEDIOL; TETRADECANE; WATER; TOCOPHEROL; COCO GLUCOSIDE; LEVOMENOL; CALENDULA OFFICINALIS FLOWER; GLYCERIN; CHAMOMILE; NASTURTIUM OFFICINALE; JOJOBA OIL, RANDOMIZED; MICROCRYSTALLINE CELLULOSE

Babo Botanicals Swim and Sport Mineral Sunscreen Spray SPF 30

Active ingredient

Zinc Oxide 14.5%

Purpose

Sunscreen

Uses

- Helps prevent sunburn.
- If used as directed with other sun protection measures (see Directions), decreases the risk of skin cancer and early skin aging caused by the sun.

Warnings

For external use only.

Do not use

on damaged or broken skin.

When using this product

- keep out of eyes. Rinse with water to remove.

Stop use and ask doctor

- if rash occurs.

Keep out of reach of children.

If swallowed, get medical help or contact a Poison Control Center immediately.

Directions

- Shake well
- Apply liberally 15 minutes before sun exposure.
- Reapply after 80 minutes of swimming or sweating, immediately after towel-drying, at least every two hours.

Sun Protection Measures Spending time in the sun increases your risk of skin cancer and early skin aging. To decrease this risk, regularly use a sunscreen with a Broad Spectrum SPF of 15 or higher and other sun protection measures including:

- Limit time in the sun, especially from 10 a.m. - 2 p.m.
- Wear long-sleeve shirts, pants, hats and sunglasses.
- Children under 6 months of age: ask a doctor

Other information

- Protect this product from excessive heat and direct sun.
- May stain some fabrics and surfaces.

Inactive ingredients

Water (Aqua), Helianthus Annuus (Sunflower) Seed Oil, Butyloctyl Salicylate, Tetradecane, Caprylic/Capric Triglyceride, Carthamus Tinctorius (Safflower) Seed Oil, Methyl Dihydroabietate, Bentonite, Cetearyl Alcohol, Propanediol, Passiflora Edulis (Maracuja) Seed Oil, Jojoba Esters, Tocopherol (Vitamin E), Glycerin, Bisabolol, Calendula Officinalis Flower Extract, Chamomilla Recutita (Matricaria) Flower Extract, Nasturtium Officinale (Watercress) Flower/Leaf Extract, Spiraea Ulmaria (Meadowsweet) Flower Extract, Microcrystalline Cellulose, Coco-Glucoside, Polyhydroxystearic Acid, Caprylhydroxamic Acid, Cellulose Gum, Caprylyl Glycol.

Questions or comments?

Call 1-800-422-2987 M-F

9:00am - 5:00pm EST